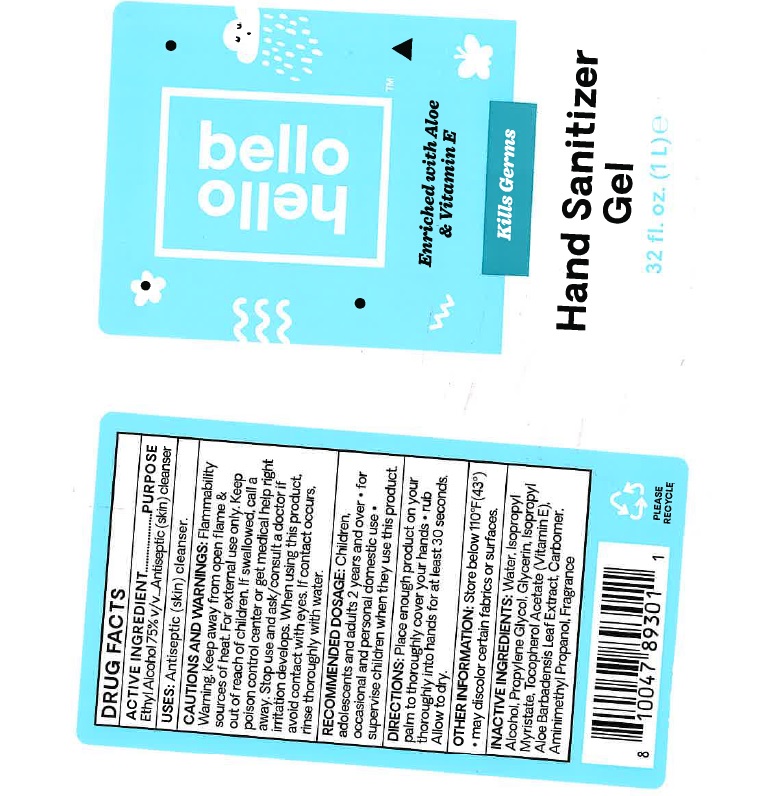 DRUG LABEL: Hello Bello
NDC: 50157-120 | Form: LIQUID
Manufacturer: Brands International Corp
Category: otc | Type: HUMAN OTC DRUG LABEL
Date: 20200818

ACTIVE INGREDIENTS: ALCOHOL 75 mL/1000 mL
INACTIVE INGREDIENTS: GLYCERIN; ISOPROPYL ALCOHOL; PROPYLENE GLYCOL; .ALPHA.-TOCOPHEROL ACETATE; WATER; ISOPROPYL MYRISTATE; ALOE VERA LEAF; AMINOMETHYLPROPANOL; CARBOMER HOMOPOLYMER, UNSPECIFIED TYPE

Hello Bello- Hand Sanitizer

ACTIVE INGREDIENT

Ethyl Alcohol 75%

Purpose -Antiseptic Skin cleanser

Use

- Antiseptic Skin cleanser

Warnings

Keep away from open flame & sources of heat.

For extenal use only.

Keep out of children

If accidently swallowed, call a posion control center or get medical help right away.

USER SAFETY WARNINGS

Do not get into eyes

If contact occurs, rinse thoroughly with water

DOSAGE AND ADMINISTRATION

- Children,adolescents and adults 2 years and over.
- for occasional and personal domestic use
- supervise children when they use this product.
- Place enough product on your plam to thoroughly cover your hands.
- rub thoroughly into hands for at least 30 seconds
- Allow to dry.

Other Information

- May discolor certain fabrics or surfaces
- do not store above 110 F (43 C)

INACTIVE INGREDIENT

Water, Isopropyl Alcohol, Glycerin, Carbomer, Aminomethyl Propanol, Fragrance, Proylene glycol, Isopropyl Myristate, Aloe Barbadensis Leaf Juice, Tocopheryl (Vitamin E) Actetate.